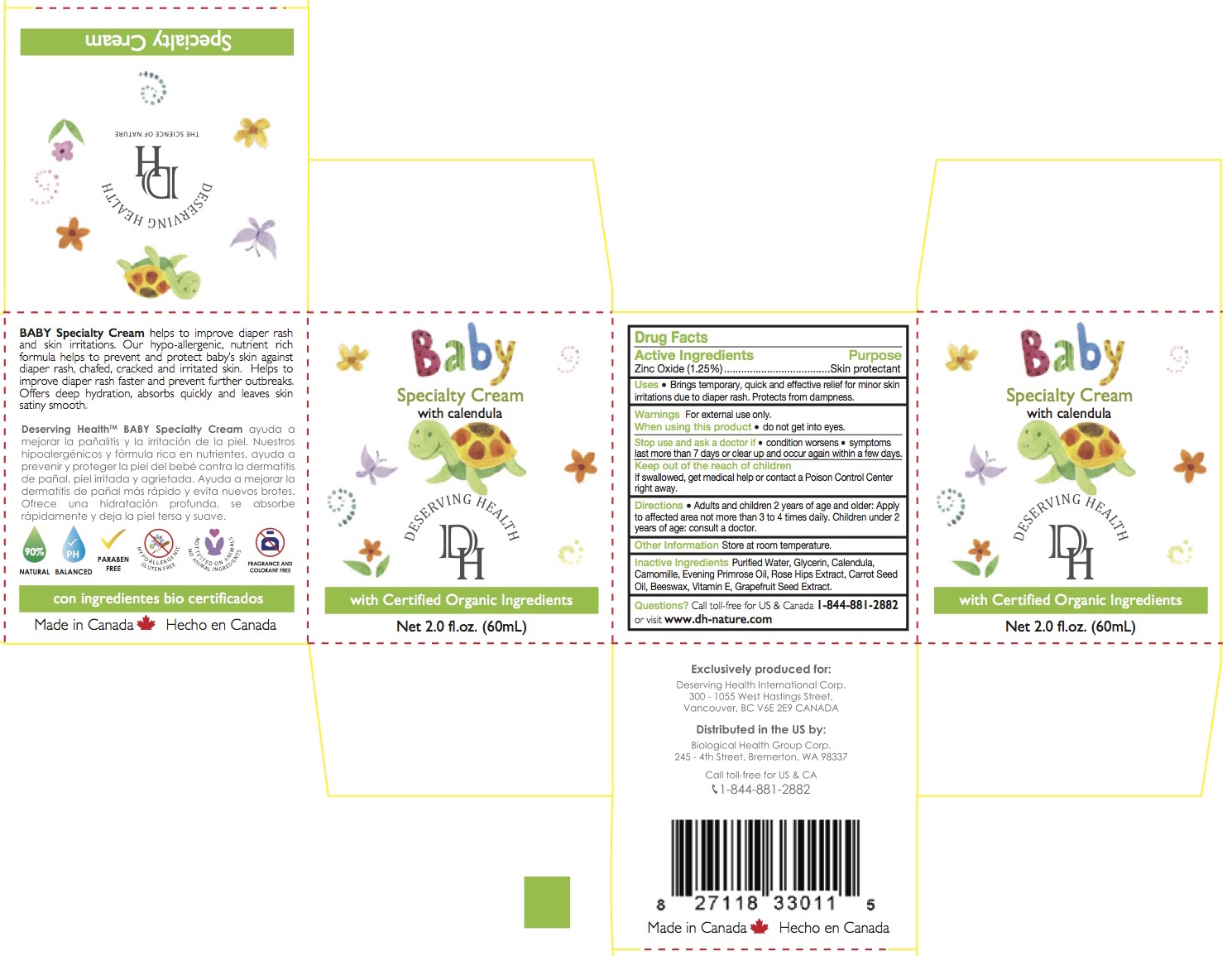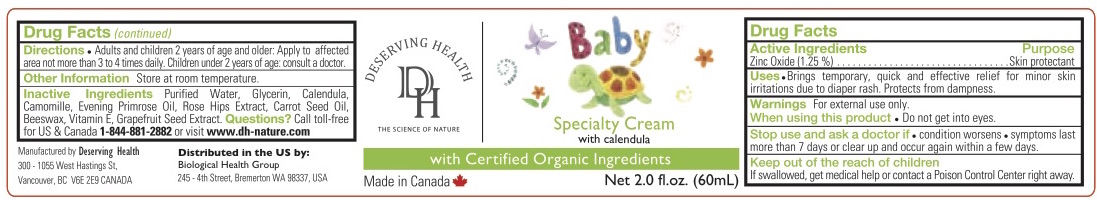 DRUG LABEL: Deserving Health Baby Specialty Cream
NDC: 69711-010 | Form: CREAM
Manufacturer: Deserving Health International Corp
Category: otc | Type: HUMAN OTC DRUG LABEL
Date: 20170721

ACTIVE INGREDIENTS: ZINC OXIDE 12 g/100 mL
INACTIVE INGREDIENTS: WATER; GLYCERIN; CALENDULA OFFICINALIS FLOWER; CHAMOMILE; EVENING PRIMROSE OIL; ROSA CANINA FRUIT OIL; CARROT SEED OIL; YELLOW WAX; .ALPHA.-TOCOPHEROL; CITRUS PARADISI SEED

Deserving Health Baby Specialty Cream

Active Ingredient

Zinc Oxide 1.25%

Purpose

Skin Protectant

Uses

- Brings temporary, quick and effective relief for minor skin irritations due to diaper rash. Protects from dampness.

Warnings

For external use only.

When using this product

- do not get into eyes.

Stop use and ask a doctor if

- condition worsens
- symptoms last more than 7 days or clear up and occur again within a few days.

Keep out of reach of children. If swallowed, get medical help or contact a Poison Control Center right away.

Directions

- Adults and children 2 years of age and older: Apply to affected area not more than 3 to 4 times daily. Children under 2 years of age: consult a doctor.

Inactive Ingredients

Purified Water, Glycerin, Calendula, Camomille, Evening Primrose Oil, Rose Hips Extract, Carrot Seed Oil, Beeswax, Vitamin E, Grapefruit Seed Extract.

Other Information

Store at room temperature.

Questions?

Call toll-free for US & Canada 844-881-2882 or visit www.dh-nature.com

PRINCIPAL DISPLAY PANEL

Baby Specialty Cream
with calendula

with Certified Organic Ingredients